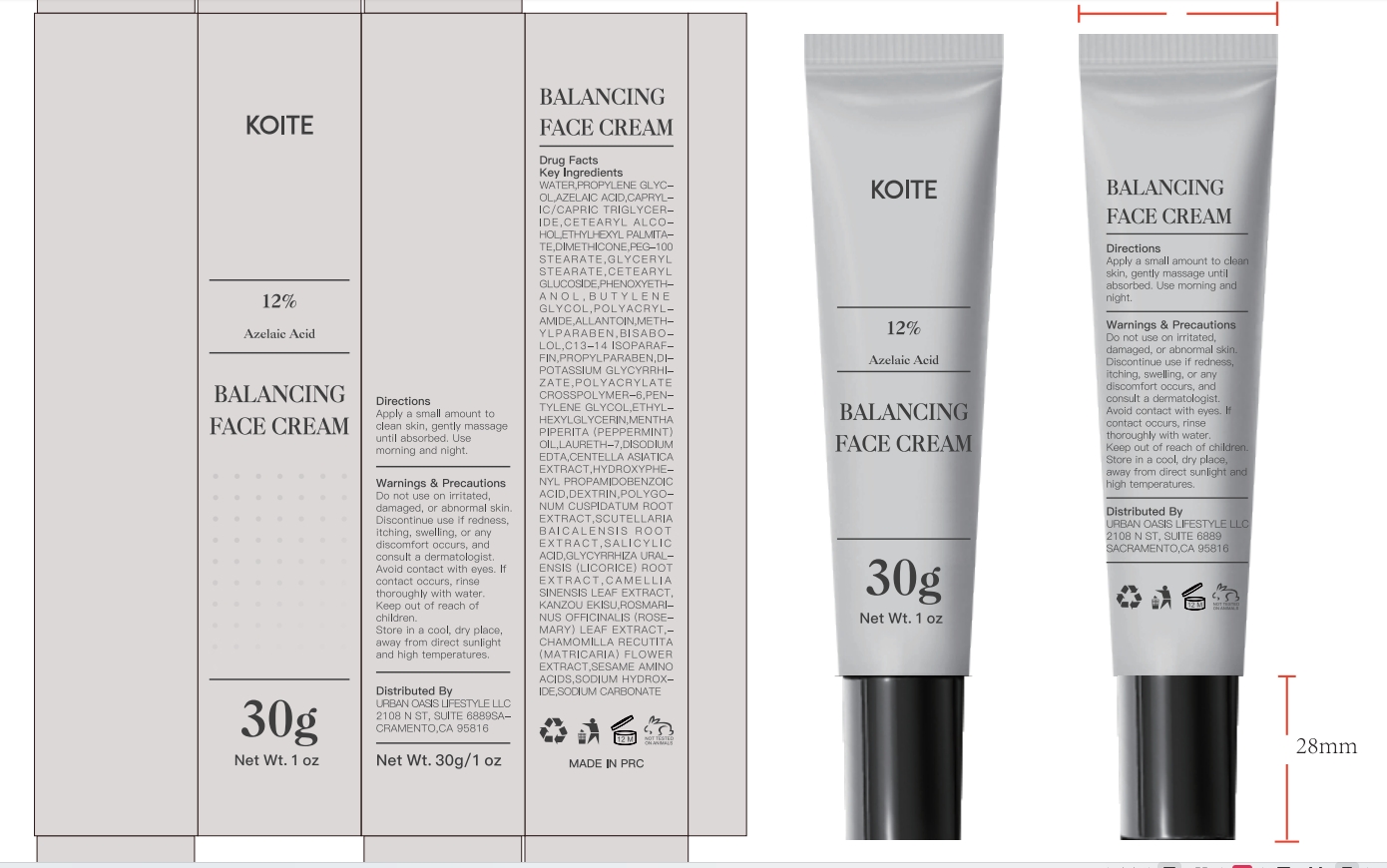 DRUG LABEL: KOITE 12% Azelaie Acid Balancing Face Cream
NDC: 84507-037 | Form: CREAM
Manufacturer: Guangdong Miaolian Cosmetics Co., Ltd.
Category: otc | Type: HUMAN OTC DRUG LABEL
Date: 20250402

ACTIVE INGREDIENTS: AZELAIC ACID 12 mg/100 g
INACTIVE INGREDIENTS: PENTYLENE GLYCOL; ALLANTOIN; BISABOLOL; DIPOTASSIUM GLYCYRRHIZATE; GLYCYRRHIZA URALENSIS ROOT; ROSMARINUS OFFICINALIS (ROSEMARY) LEAF OIL; ETHYLHEXYL PALMITATE; PEG-100 STEARATE; SODIUM CARBONATE; SALICYLIC ACID; LAURETH-7; MENTHA PIPERITA (PEPPERMINT) OIL; CETEARYL GLUCOSIDE; WATER; PROPYLENE GLYCOL; POLYACRYLAMIDE (1500 MW); C13-14 ISOPARAFFIN; DIMETHICONE; GLYCERYL STEARATE; SODIUM HYDROXIDE; PHENOXYETHANOL; POLYGONUM CUSPIDATUM ROOT; CAMELLIA SINENSIS LEAF; MATRICARIA CHAMOMILLA; METHYLPARABEN; PROPYLPARABEN; EDETATE DISODIUM; ARGININE; GLYCYRRHIZA GLABRA (LICORICE) ROOT; CETEARYL ALCOHOL; CENTELLA ASIATICA ROOT; HYDROXYPHENYL PROPAMIDOBENZOIC ACID; SCUTELLARIA BAICALENSIS ROOT; CYCLODEXTRIN; CAPRYLIC/CAPRIC TRIGLYCERIDE; BUTYLENE GLYCOL; POLYACRYLATE CROSSPOLYMER-6; ETHYLHEXYLGLYCERIN

WARNINGS

For external use only, avoid the eye area. Avoid direct sunlight during use.
Discontinue use immediately if irritation occurs. Store in a cool, dry place.

PURPOSE

Evens skin tone & fades spots.
Balances oil & prevents breakouts.

Keep out of reach of children.

ACTIVE INGREDIENT

AZELAIC ACID ----12%

INACTIVE INGREDIENT

WATER
PROPYLENE GLYCOL
CAPRYLIC/CAPRIC TRIGLYCERIDE
ETHYLHEXYL PALMITATE
CETEARYL ALCOHOL
CETEARYL GLUCOSIDE
POLYACRYLAMIDE
C13-14 ISOPARAFFIN
LAURETH-7
DIMETHICONE
GLYCERYL STEARATE
PEG-100 STEARATE
SODIUM HYDROXIDE
SODIUM CARBONATE
POLYACRYLATE CROSSPOLYMER-6
PHENOXYETHANOL
ETHYLHEXYLGLYCERIN
BUTYLENE GLYCOL
CENTELLA ASIATICA EXTRACT
SCUTELLARIA BAICALENSIS ROOT EXTRACT
POLYGONUM CUSPIDATUM ROOT EXTRACT
CAMELLIA SINENSIS LEAF EXTRACT
KANZOU EKISU
CHAMOMILLA RECUTITA (MATRICARIA) FLOWER EXTRACT
ROSMARINUS OFFICINALIS (ROSEMARY) LEAF EXTRACT
PENTYLENE GLYCOL
HYDROXYPHENYL PROPAMIDOBENZOIC ACID
METHYLPARABEN
ALLANTOIN
BISABOLOL
PROPYLPARABEN
DIPOTASSIUM GLYCYRRHIZATE
GLYCYRRHIZA URALENSIS (LICORICE) ROOT EXTRACT
MENTHA PIPERITA (PEPPERMINT) OIL
DISODIUM EDTA
HYDROXYPROPYL CYCLODEXTRIN
SALICYLIC ACID
ARGININE

INDICATIONS AND USAGE

Apply a thin layer to cleansed face or affected areas morning and evening. Avoid the eye area. Use
sunscreen during the day.

When using this product, avoid contact with eyes. If contact occurs,
rinse thoroughly with water. Discontinve use if any irritation or adverse reaction occurs.